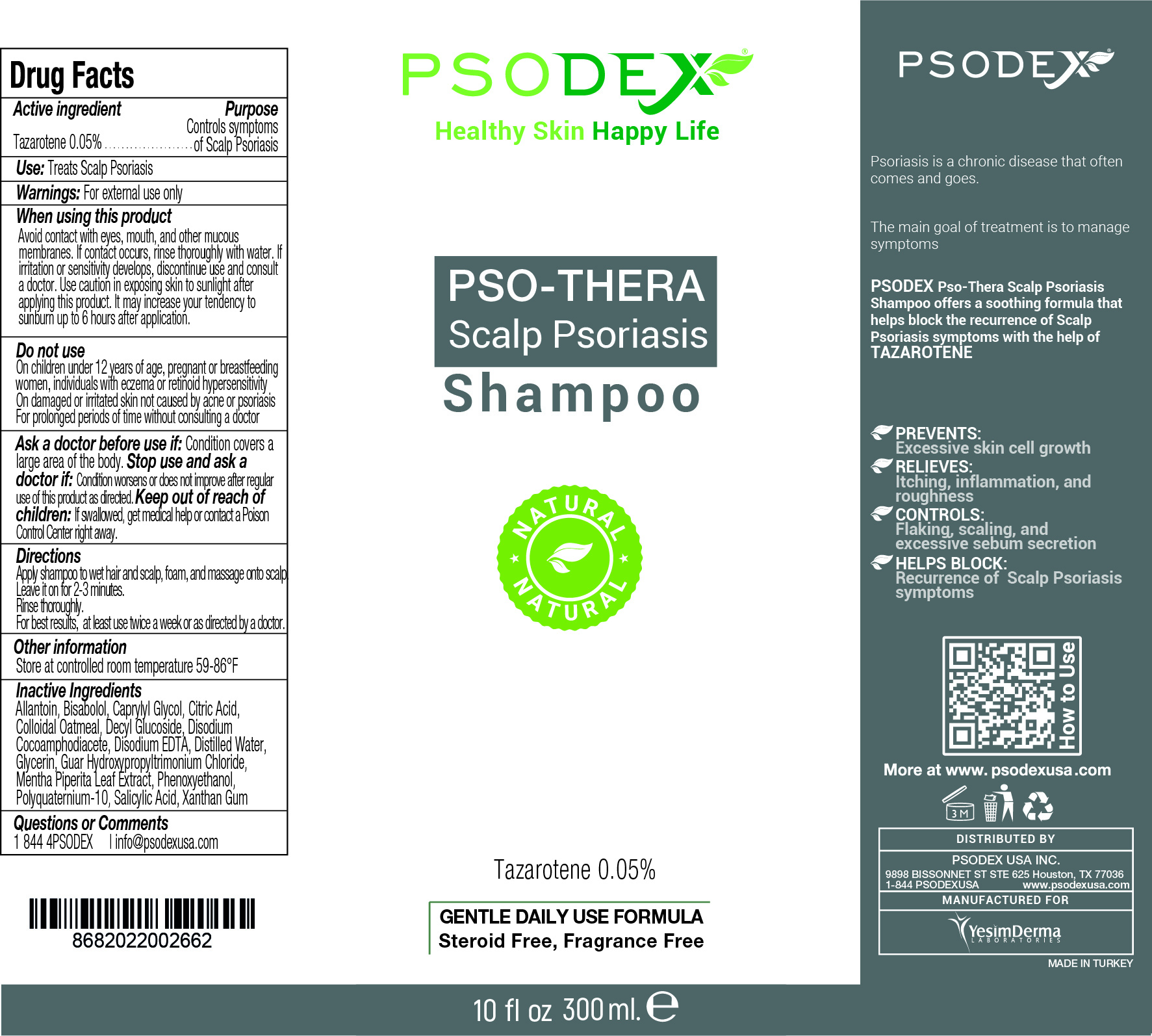 DRUG LABEL: PSO THERA
NDC: 73503-011 | Form: SHAMPOO
Manufacturer: PSODEX USA INC
Category: otc | Type: HUMAN OTC DRUG LABEL
Date: 20231221

ACTIVE INGREDIENTS: TAZAROTENE 0.05 g/100 mL
INACTIVE INGREDIENTS: DECYL GLUCOSIDE 10 g/100 mL; MENTHA PIPERITA LEAF 5 g/100 mL; LEVOMENOL 5 g/100 mL; ALLANTOIN 5 g/100 mL; PHENOXYETHANOL 0.5 g/100 mL; CAPRYLYL GLYCOL 0.5 g/100 mL; GUAR HYDROXYPROPYLTRIMONIUM CHLORIDE (1.7 SUBSTITUENTS PER SACCHARIDE) 0.5 g/100 mL; WATER 47.35 mL/100 mL; DISODIUM COCOAMPHODIACETATE 20 g/100 mL; XANTHAN GUM 0.3 g/100 mL; EDETATE DISODIUM ANHYDROUS 0.5 g/100 mL; CITRIC ACID MONOHYDRATE 0.3 g/100 mL; OATMEAL 1 g/100 mL; SALICYLIC ACID 1.5 g/100 mL; POLYQUATERNIUM-10 (1000 MPA.S AT 2%) 0.5 g/100 mL; GLYCERIN 2 g/100 mL

PSO THERA Scalp Psoriasis Shampoo

PSO-THERA Scalp Psoriasis Shampoo

Psoriasis is a chronic disease that often comes and goes.

The main goal of treatment is to manage symptoms

PSODEX Pso-Thera Scalp Psoriasis Shampoo offers a soothing formula that helps block the recurrence of Scalp Psoriasis symptoms with the help of TAZAROTENE

PREVENTS:
Excessive skin cell growth

RELIEVES:
Itching, inflammation, and roughness

CONTROLS:
Flaking, scaling, and excessive sebum secretion

HELPS BLOCK:
Recurrence of Scalp Psoriasis symptoms

PSO-THERA Scalp Psoriasis Shampoo

Inactive Ingredients:

Allantoin, Bisabolol, Caprylyl Glycol, Citric Acid, Colloidal Oatmeal, Decyl Glucoside, Disodium Cocoamphodiacete, Disodium EDTA, Distilled Water, Glycerin, Guar Hydroxypropyltrimonium Chloride, Mentha Piperita Leaf Extract, Phenoxyethanol, Polyquaternium-10, Salicylic Acid, Xanthan Gum

PSO-THERA Scalp Psoriasis Shampoo

Use:

Treats Scalp Psoriasis

PSO-THERA Scalp Psoriasis Shampoo

DISTRIBUTED BY: Psodex USA Inc.

9898 Bissonnet St Ste 625 Houston, TX 77036

1-844 4PSODEX www.psodexusa.com

MANUFACTURED FOR

Yesim Derma Laboratories

PSO-THERA Scalp Psoriasis Shampoo

Directions:

Apply shampoo to wet hair and scalp, foam, and massage onto scalp.
Leave it on for 2-3 minutes.
Rinse thoroughly.
For best results, at least use twice a week or as directed by a doctor.

PSO-THERA Scalp Psoriasis Shampoo

Active ingredient:

Tazarotene 0.05%

PSO-THERA Scalp Psoriasis Shampoo

Ask a doctor before use if: Condition covers a
large area of the body.

PSO-THERA Scalp Psoriasis Shampoo

Keep out of reach of children: If swallowed, get medical help or contact a Poison Control Center right away.

PSO-THERA Scalp Psoriasis Shampoo

Stop use and ask a doctor if: Condition worsens or does not improve after regular use of this product as directed.

PSO-THERA Scalp Psoriasis Shampoo

Do not use:

On children under 12 years of age, pregnant or breastfeeding women, individuals with eczema or retinoid hypersensitivity
On damaged or irritated skin not caused by acne or psoriasis
For prolonged periods of time without consulting a doctor

PSO-THERA Scalp Psoriasis Shampoo

Purpose:

Controls symptoms of Scalp Psoriasis

PSO-THERA Scalp Psoriasis Shampoo

Questions or Comments: 1 844 4PSODEX | info@psodexusa.com

PSO-THERA Scalp Psoriasis Shampoo

When using this product:

Avoid contact with eyes, mouth, and other mucous membranes. If contact occurs, rinse thoroughly with water. If irritation or sensitivity develops, discontinue use and consult a doctor. Use caution in exposing skin to sunlight after applying this product. It may increase your tendency to sunburn up to 6 hours after application.

PSO-THERA Scalp Psoriasis Shampoo

Other information : Store at controlled room temperature 59-86°F

PSO-THERA Scalp Psoriasis Shampoo

Warnings: For external use only

PSO-THERA Scalp Psoriasis Shampoo

Tazarotene 0.05%